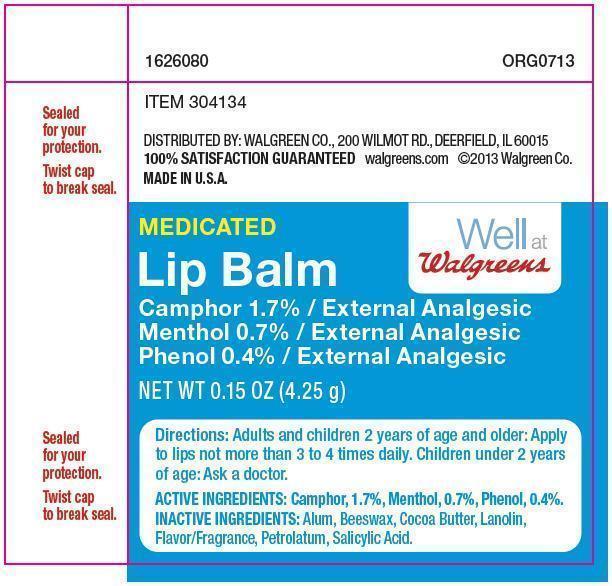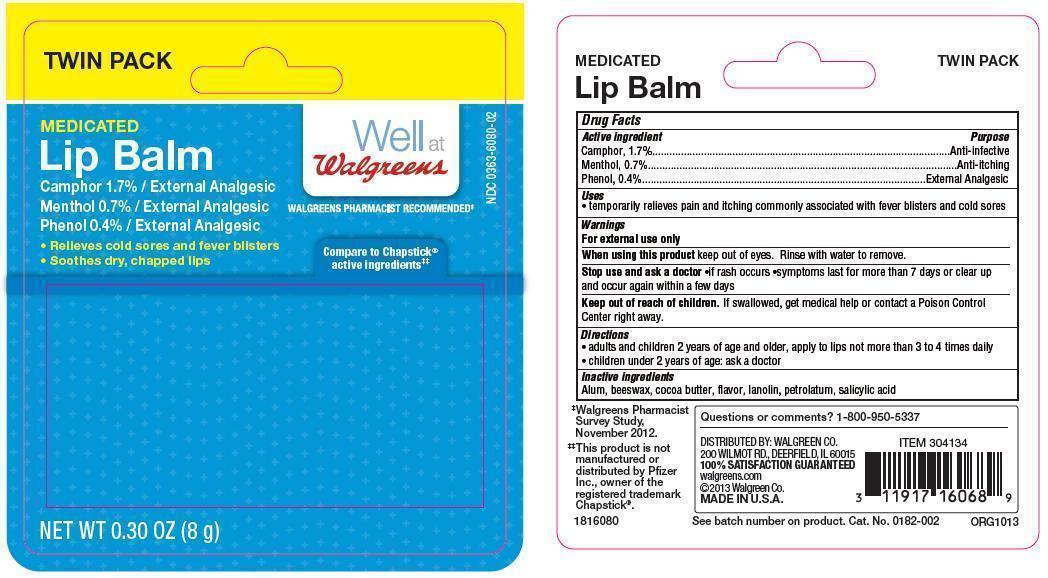 DRUG LABEL: Medicated Lip Balm
NDC: 0363-6080 | Form: STICK
Manufacturer: Walgreen Co
Category: otc | Type: HUMAN OTC DRUG LABEL
Date: 20131115

ACTIVE INGREDIENTS: CAMPHOR (NATURAL) 1.7 mg/1 g; MENTHOL 0.7 mg/1 g; PHENOL 0.4 mg/1 g
INACTIVE INGREDIENTS: ALUM, POTASSIUM; WHITE WAX; COCOA BUTTER; LANOLIN; PETROLATUM; SALICYLIC ACID

Drug Facts

Active ingredients

Camphor, 1.7%

Menthol, 0.7%

Phenol, 0.4%

Purpose

External Analgesic

Uses

- temporarily relieves pain and itching commonly associated with fever blisters and cold sores

Warnings

For external use only

When using this product keep out of eyes. Rinse with water to remove.

Stop use and ask a doctor

- if rash occurs
- symptoms last for more than 7 days or clear up and occur agin within a few days

Keep out of reach of children. If swallowed, get medical help or contact a Poison Control Center right away.

Directions

- adults and children 2 years of age and older, apply to lips not more than 3 to 4 times daily
- children under 2 years of age: ask a doctor

Inactive ingredients

Alum, beeswax, cocoa butter, flavor, lanolin, petrolatum, salicylic acid